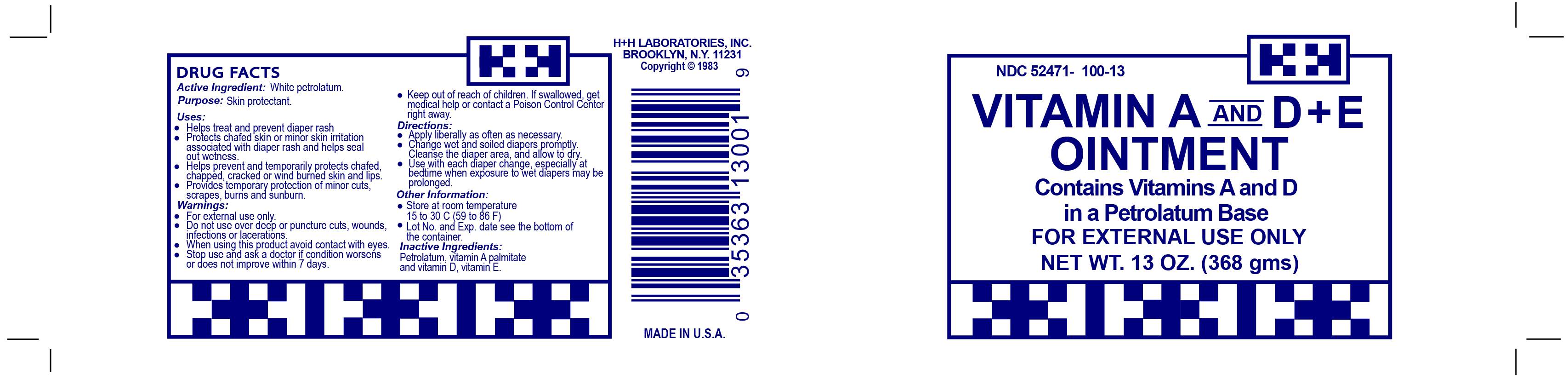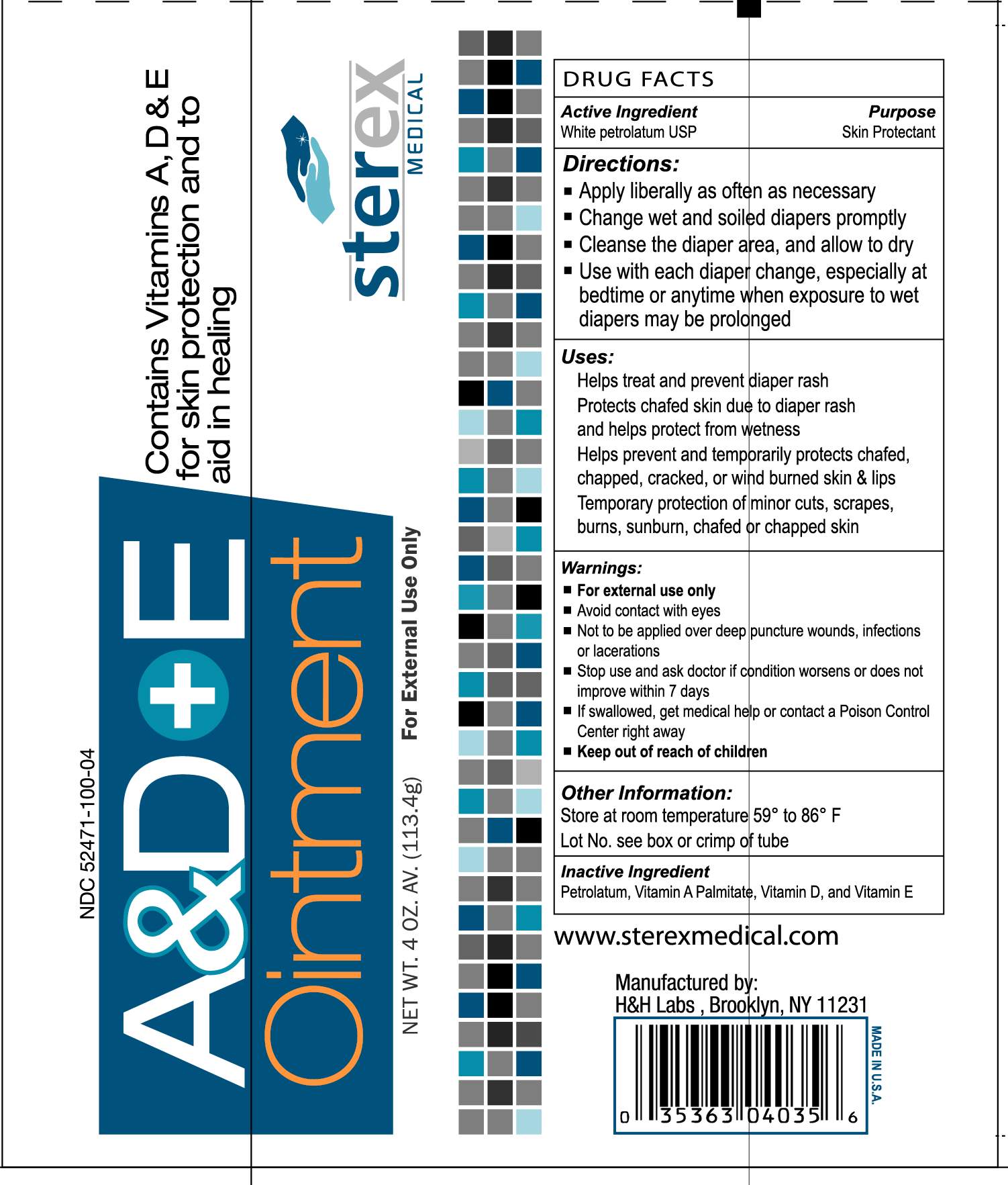 DRUG LABEL: A and D plus E
NDC: 52471-100 | Form: OINTMENT
Manufacturer: H&H Laboratories, Inc.
Category: otc | Type: HUMAN OTC DRUG LABEL
Date: 20120514

ACTIVE INGREDIENTS: PETROLATUM 937.5 mg/1 g
INACTIVE INGREDIENTS: VITAMIN A PALMITATE; ERGOCALCIFEROL

DRUG FACTS

Active Ingredient (in each gram): White Petrolatum 93.5%

Purpose-Skin Protectant

INDICATIONS AND USAGE

Uses-Temporarily protects minor cuts, scrapes, and sunburn. Helps treat and prevent diaper rash. Protects chafed skin or minor skin irritation associated with diaper rash and helps seal out wetness. Temporarily protects and helps chapped or cracked skin and lips. Helps protect lips from drying effects of wind and cold weather.

DOSAGE AND ADMINISTRATION

Directions: Apply liberally as needed Change wet and soiled diapers promptly. Cleanse the diaper area and allow to dry. Use with each diaper change, especially at bedtime when exposure to wet diapers may be prolonged.

Keep out of reach of children. If swallowed, get medical help or contact a Poison Control Center right away.

WARNINGS

For external use only. Do not use in eyes, on deep puncture wounds, animal bites, or serious burns or for more than 1 week unless directed by a doctor.

Stop use and ask a doctor if: A rash or allergic reaction develops. Condition worsens, persists, or recurs.

INACTIVE INGREDIENT

Inactive Ingredients: Corn Oil, Light Mineral Oil, Vitamin A Palmitate, Vitamin D, Vitamin E

PACKAGE LABEL

MM1

MM2